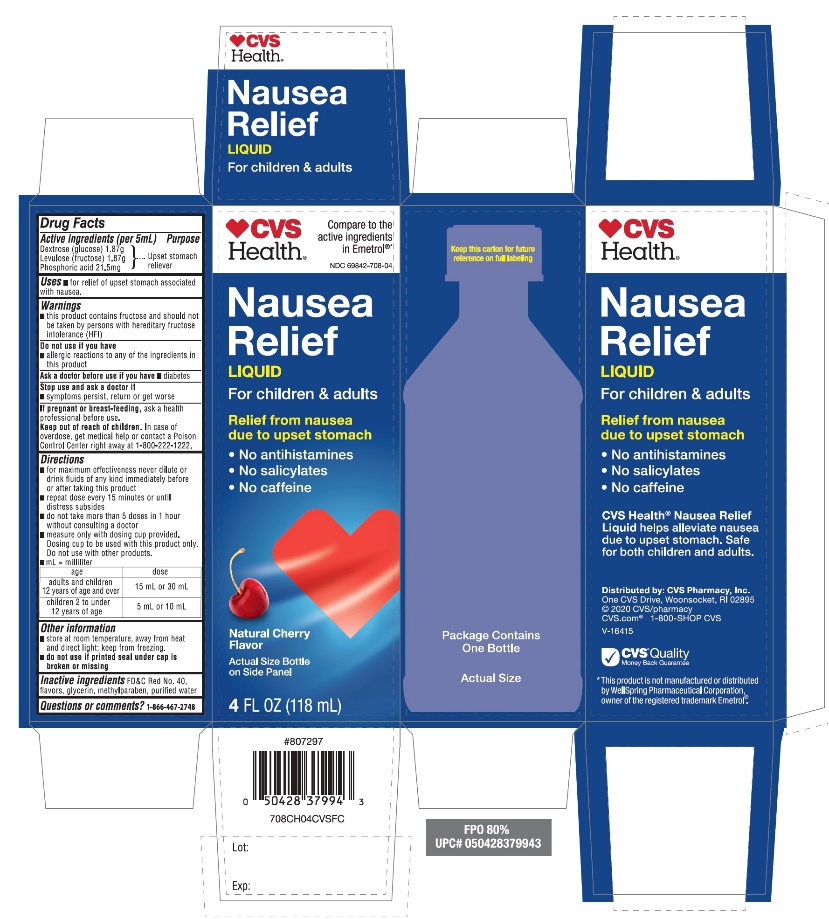 DRUG LABEL: CVS Anti Nausea

NDC: 69842-708 | Form: LIQUID
Manufacturer: CVS PHARMACY
Category: otc | Type: HUMAN OTC DRUG LABEL
Date: 20251209

ACTIVE INGREDIENTS: DEXTROSE, UNSPECIFIED FORM 1.87 g/5 mL; FRUCTOSE 1.87 g/5 mL; PHOSPHORIC ACID 21.5 mg/5 mL
INACTIVE INGREDIENTS: FD&C RED NO. 40; GLYCERIN; METHYLPARABEN; WATER

CVS Health®Nausea Relief Liquid 4FL OZ (118mL) Cherry Flavor

Active ingredients (per 5 mL)

Dextrose (glucose) 1.87 g

Levulose (fructose) 1.87 g

- Phosphoric acid 21.5 mg

Purpose

Upset Stomach Reliever

Uses

- for relief of upset stomach associated with nausea

Warnings

- this product contains fructose and should not be taken by persons with hereditary fructose intolerance (HFI).

Do not use if you have

- allergic reactions to any of the ingredients in this product

Ask a doctor before use if you have

- diabetes

Stop use and ask a doctor if

- symptoms persist, return or get worse

If pregnant or breast-feeding,

ask a health professional before use.

Keep out of reach of children.

In case of overdose, get medical help or contact a Poison Control Center right away at (1-800-222-1222)

Directions

- for maximum effectiveness never dilute or drink fluids of any kind immediately before or after taking this product
- repeat dose every 15 minutes or until distress subsides
- do not take more than 5 doses in 1 hour without consulting a doctor
- measure only with dosing cup provided. Dosing cup to be used with this product only. Do not use with other products.
- mL= milliliter

1. Age

1. dose

1. adults and children 12 years of age and over

1. 15 mL or 30 mL

1. children 2 to under 12 years of age

1. 5 ml or 10 mL

Other information

- store at room temperature away from heat and direct light; keep from freezing
- do not use if printed seal under cap is broken or missing

Inactive ingredients

FD&C Red No. 40, flavors, glycerin, methylparaben, purified water.

Questions or Comments?

1-866-467-2748

CVS Health®

NDC 69842-708-04

Compare to the active ingredients Emetrol®*

Nausea Relief

Liquid

For children & adults

Relief from nausea due to upset stomach

- No antihistamines
- No salicylates
- No caffeine

Natural Cherry Flavor

4 FL OZ (118 mL)

Package Contains One Bottle

CVS Health® Nausea Relief Liquid helps alleviate nausea due to upset stomach. Safe for both children and adults.

IMPORTANT:Keep this carton for future reference on full labeling.

Distributed by: CVS Pharmacy, Inc.

One CVS Drive, Woonsocket, RI 02895

© 2020 CVS/pharmacy

CVS.com 1-800-SHOP CVS

V-16415

CVS® Quality

Money Back Guarantee

*This product is not manufactured or distributed by Wellspring Pharmaceutical Corporation., owner of the registered trademark Emetrol®.